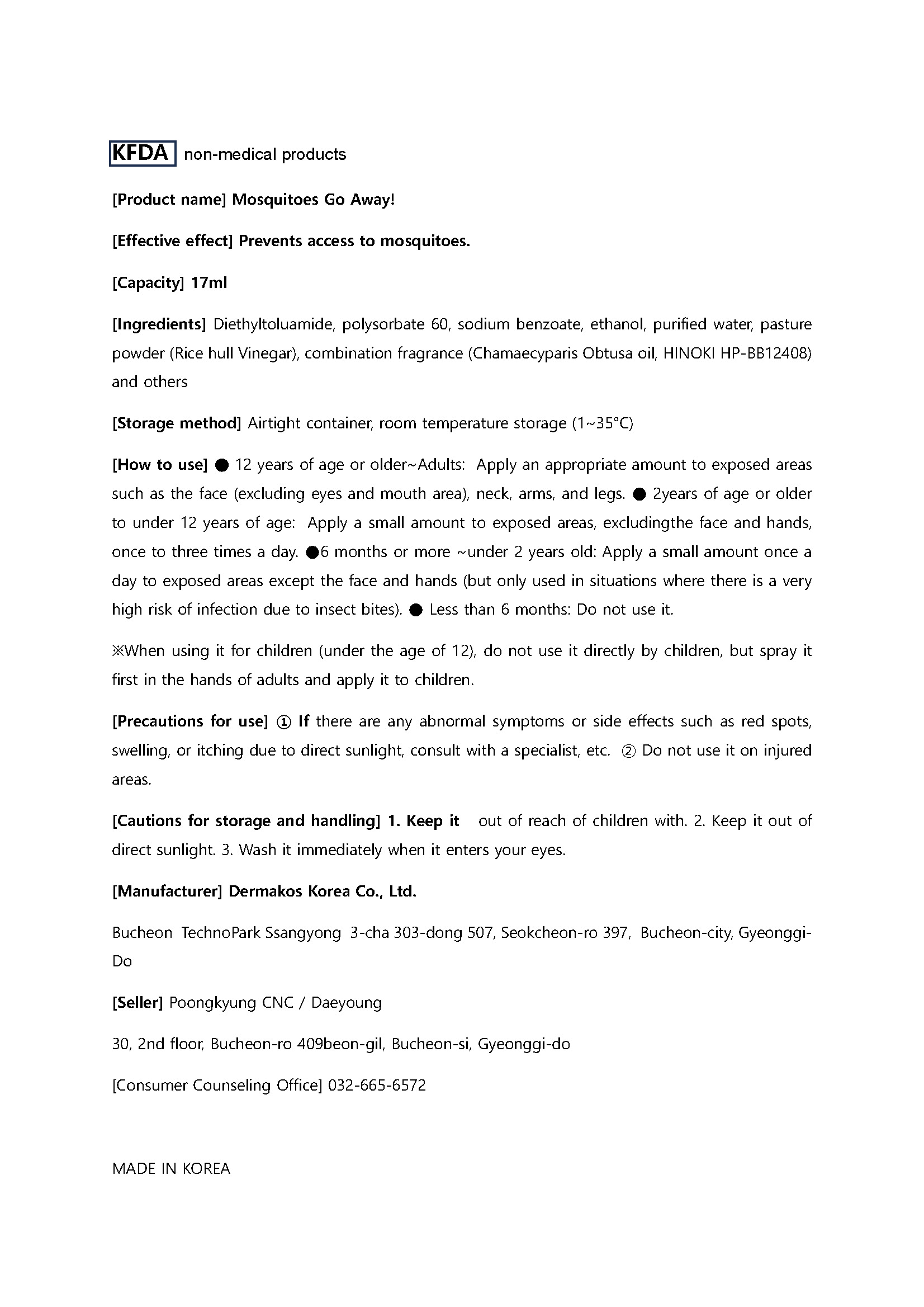 DRUG LABEL: Mosquitoes Go Away
NDC: 84442-0001 | Form: LIQUID
Manufacturer: Poongkyung CNC Corp.
Category: otc | Type: HUMAN OTC DRUG LABEL
Date: 20240624

ACTIVE INGREDIENTS: CHAMAECYPARIS OBTUSA WOOD OIL 25.5 g/100 mL
INACTIVE INGREDIENTS: WATER

Drug Facts

ACTIVE INGREDIENT

Chamaecyparis Obtusa oil

INACTIVE INGREDIENT

Diethyltoluamide, polysorbate 60, sodium benzoate, ethanol, purified water, pasture powder (Rice hull Vinegar), combination fragrance (Chamaecyparis Obtusa oil, HINOKI HP-BB12408)

PURPOSE

Prevents access to mosquitoes.

keep out of reach of the children

INDICATIONS AND USAGE

Apply a small amount to exposed areas, excludingthe face and hands, once to three times a day

WARNINGS

● 12 years of age or older~Adults: Apply an appropriate amount to exposed areas
such as the face (excluding eyes and mouth area), neck, arms, and legs. ● 2years of age or older
to under 12 years of age: Apply a small amount to exposed areas, excludingthe face and hands,
once to three times a day. ●6 months or more ~under 2 years old: Apply a small amount once a
day to exposed areas except the face and hands (but only used in situations where there is a very
high risk of infection due to insect bites). ● Less than 6 months: Do not use it.

① If there are any abnormal symptoms or side effects such as red spots,
swelling, or itching due to direct sunlight, consult with a specialist, etc. ② Do not use it on injured
areas.

DOSAGE AND ADMINISTRATION

topical use only